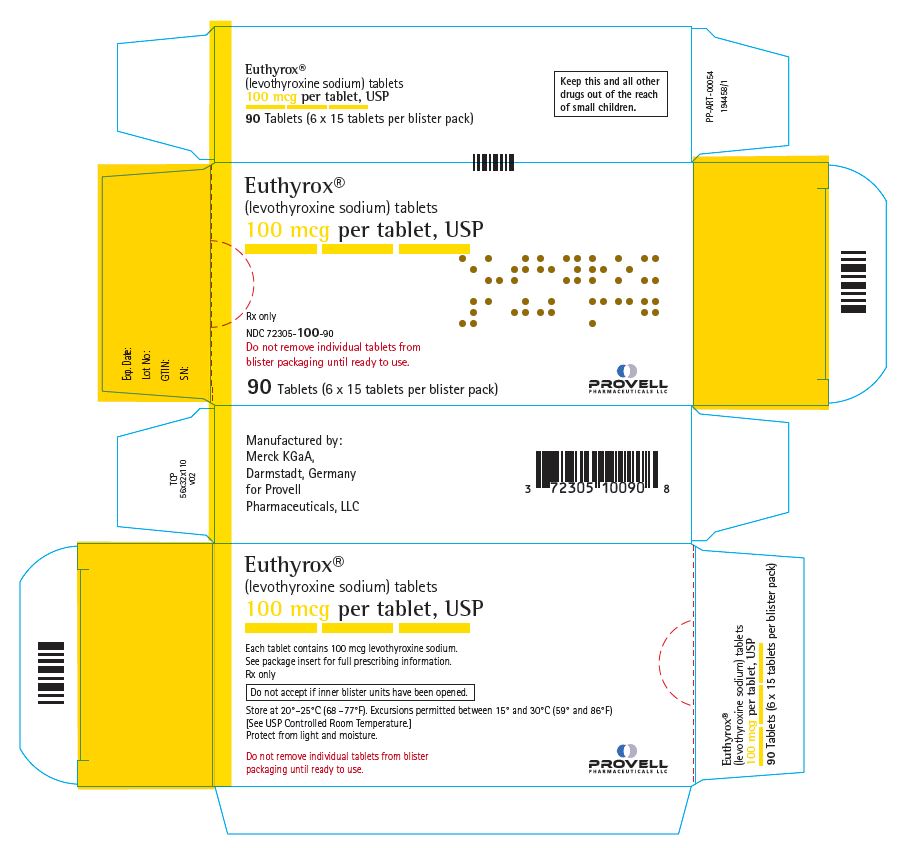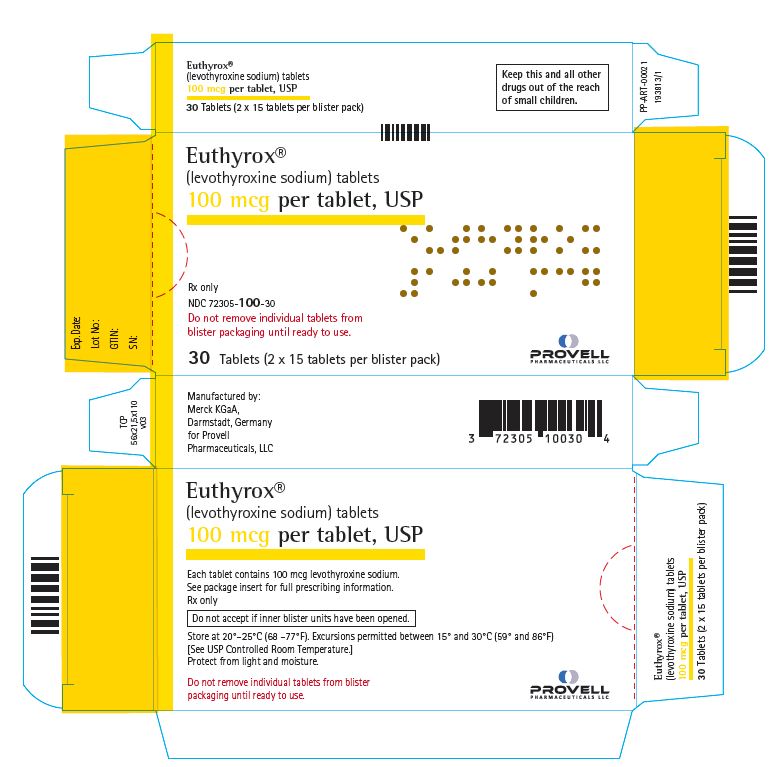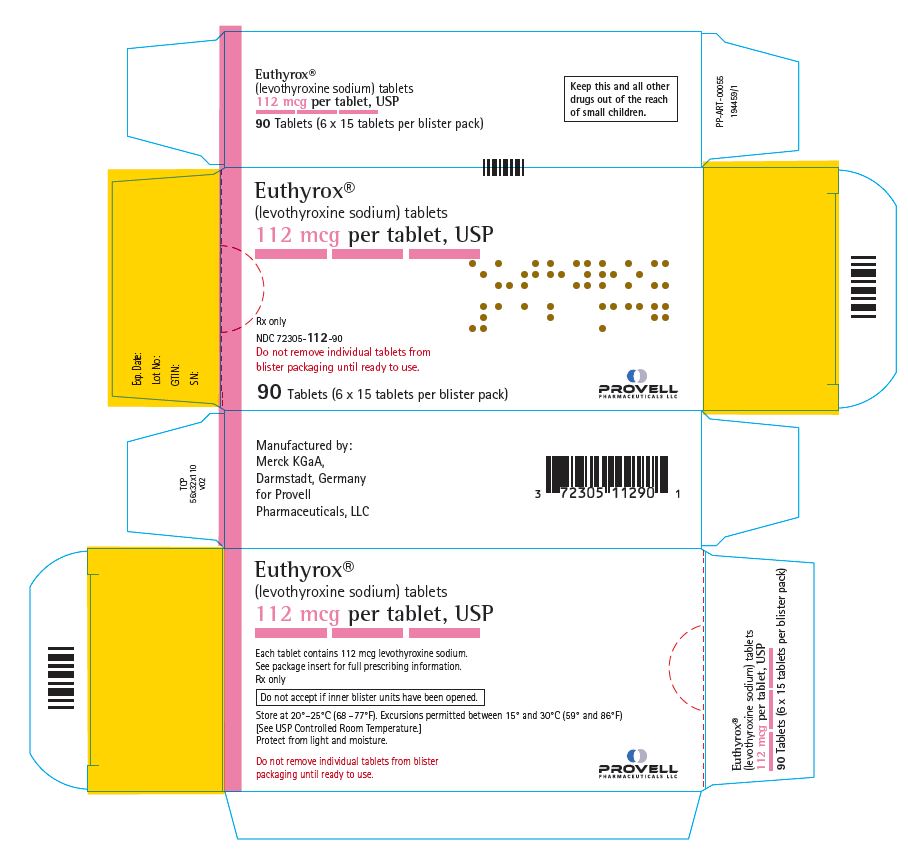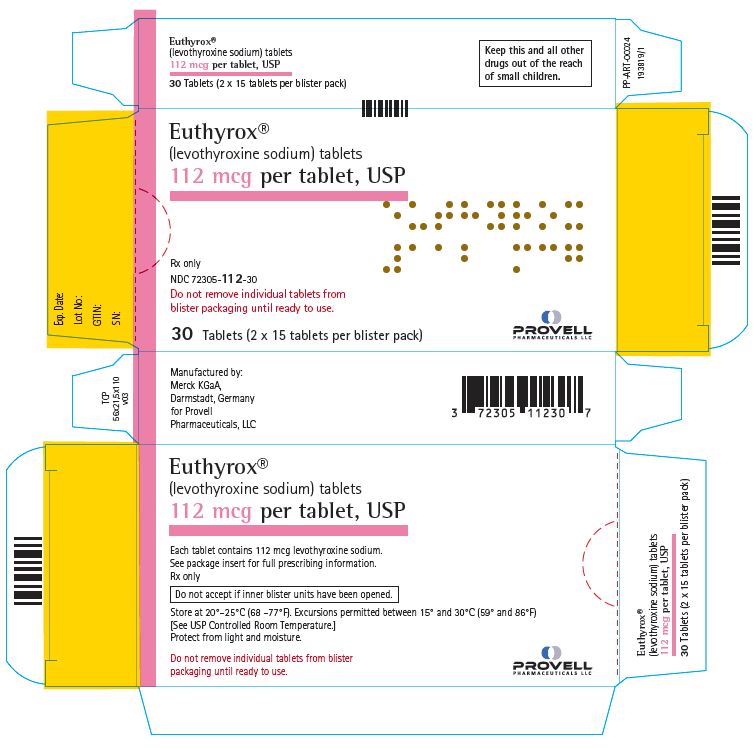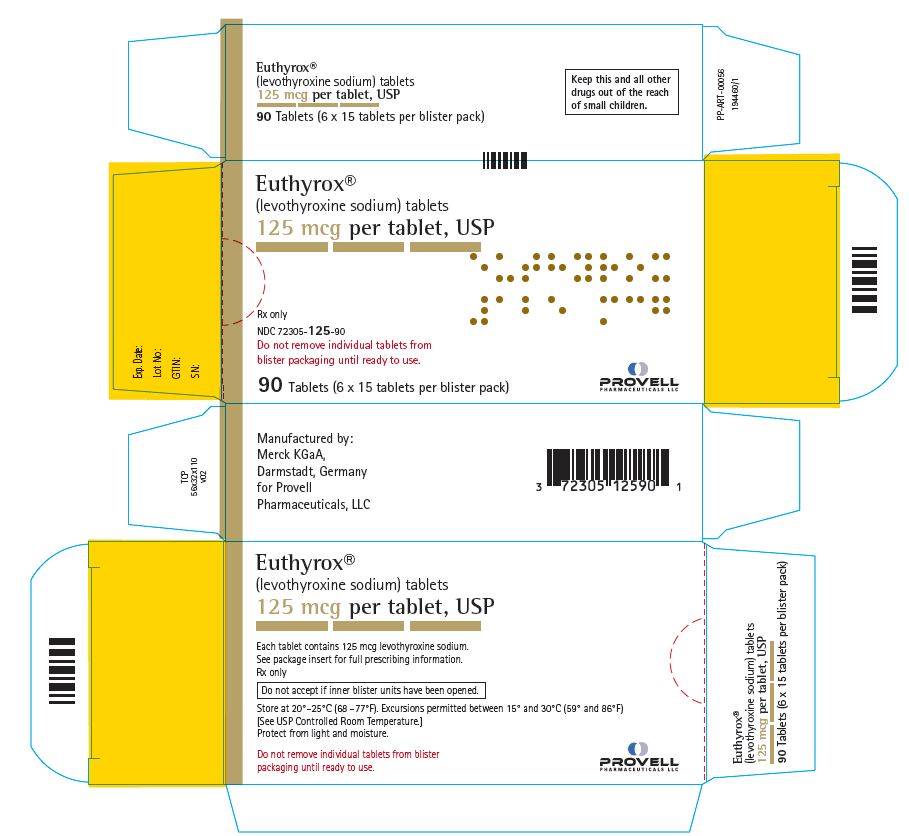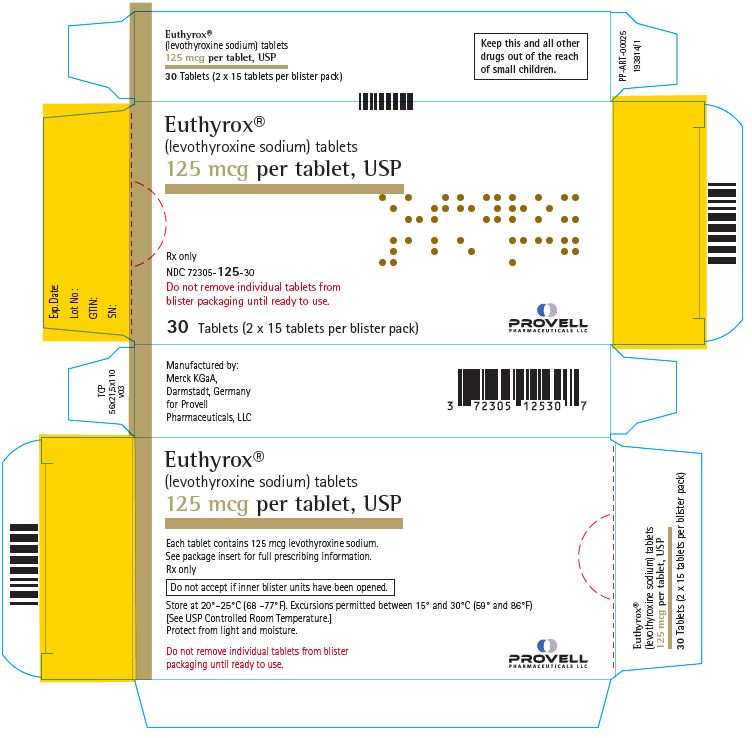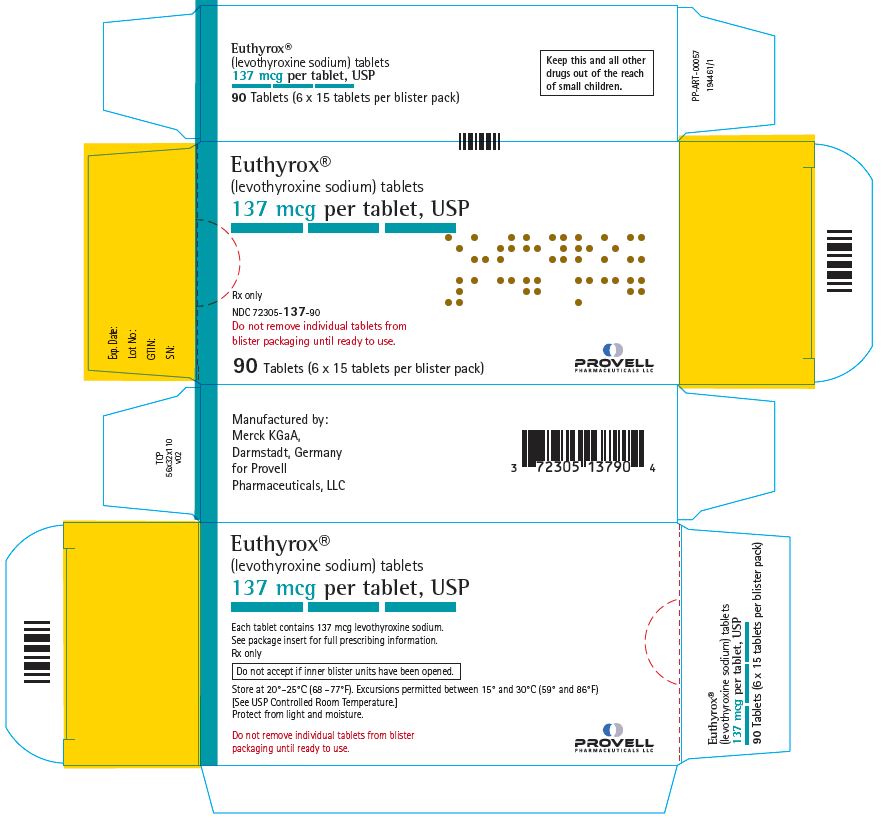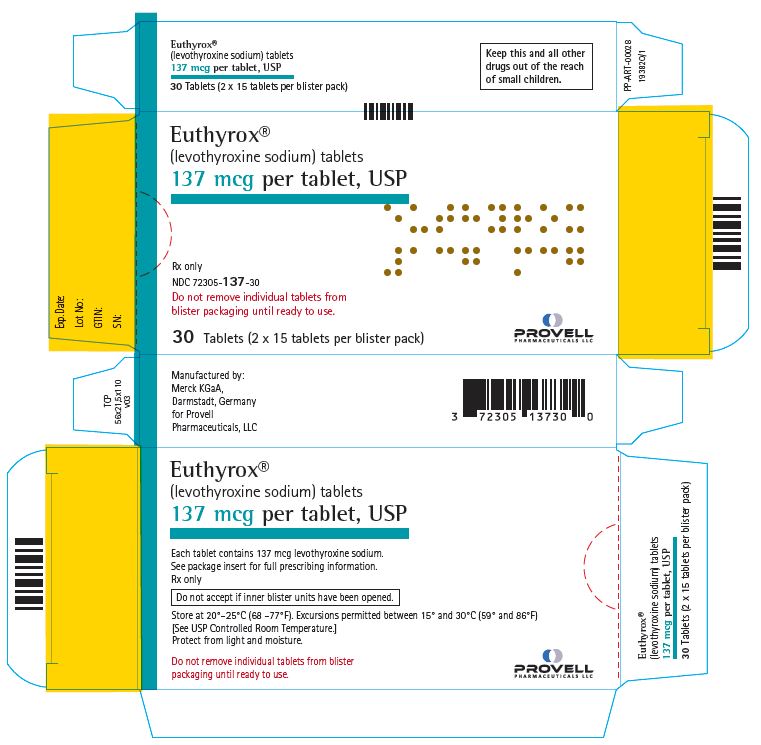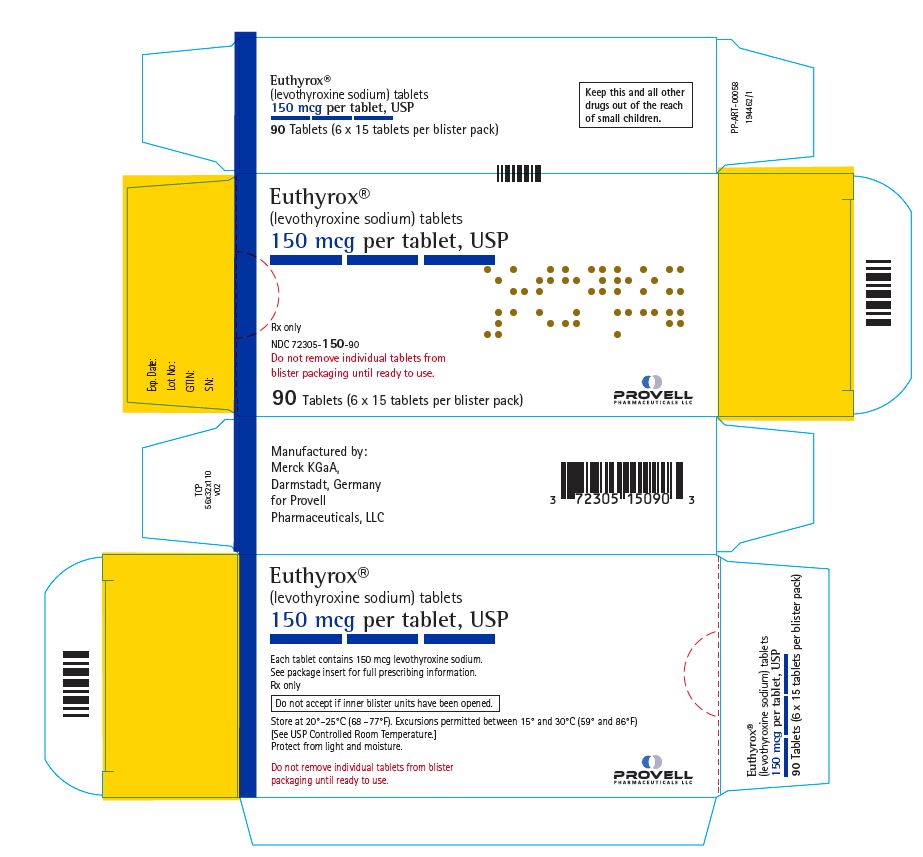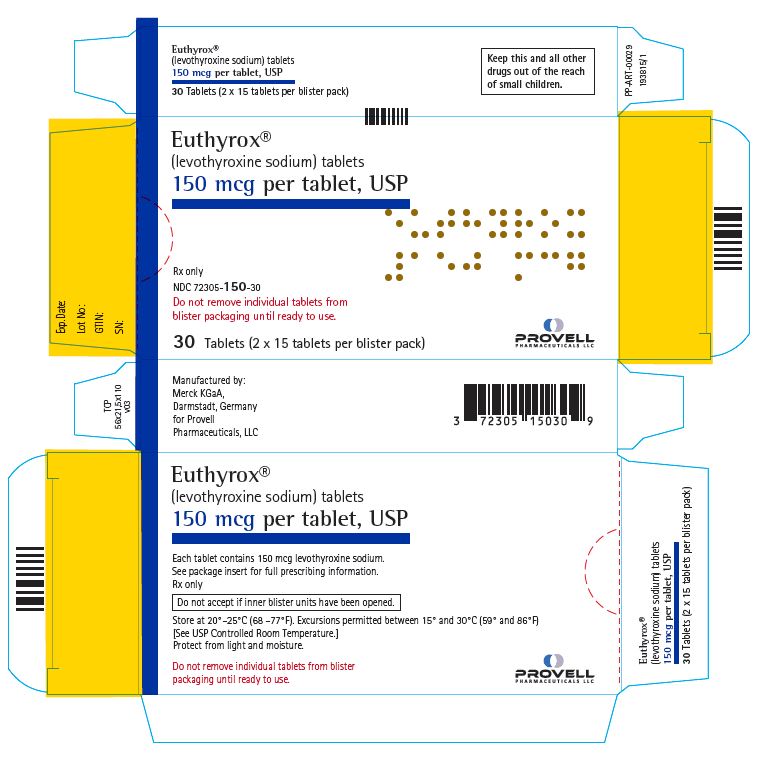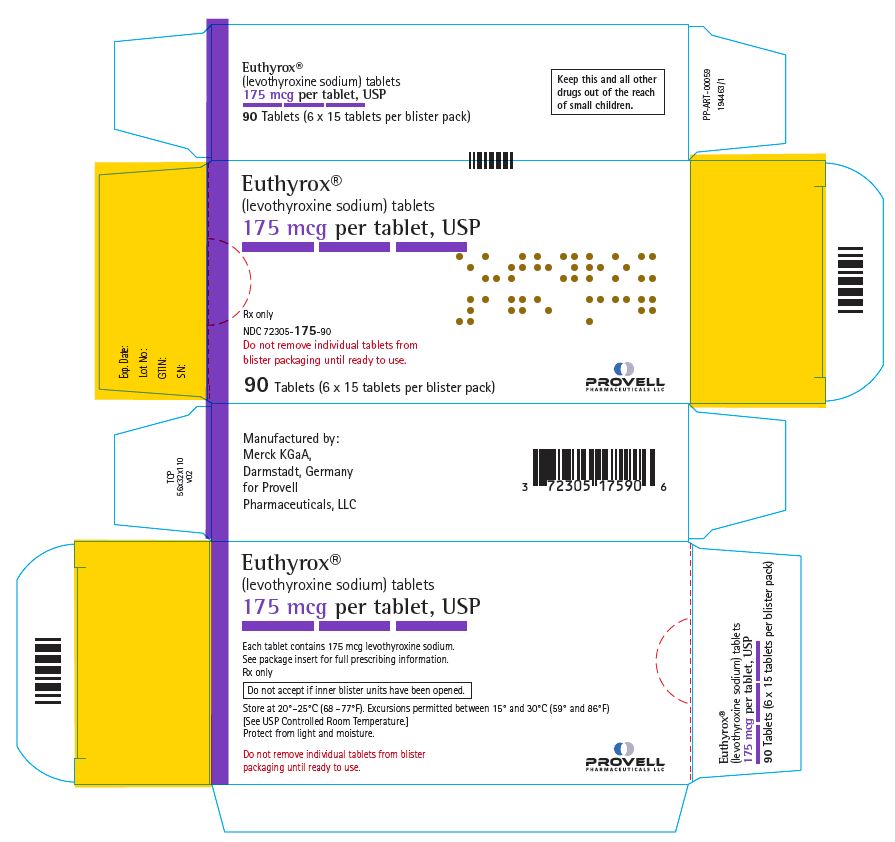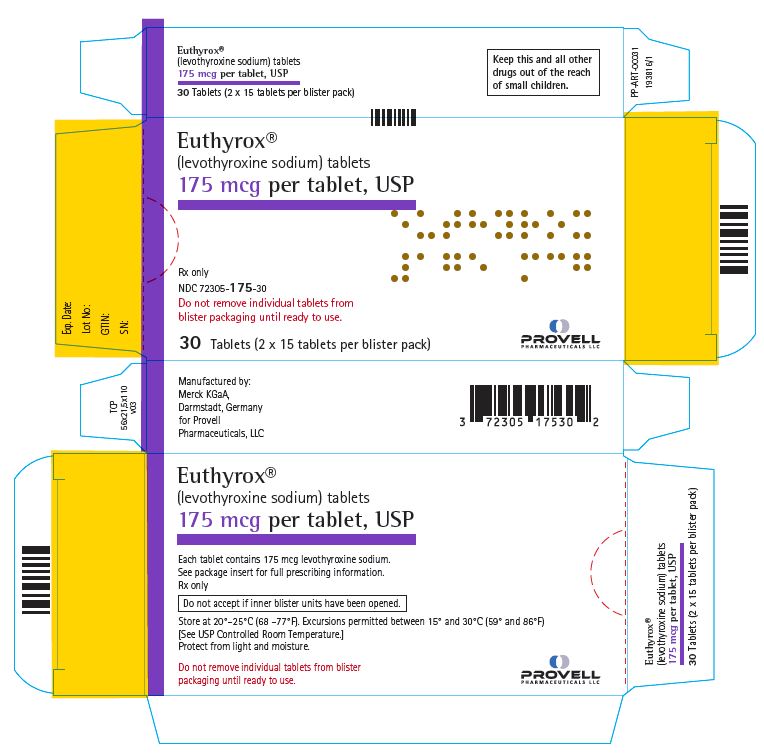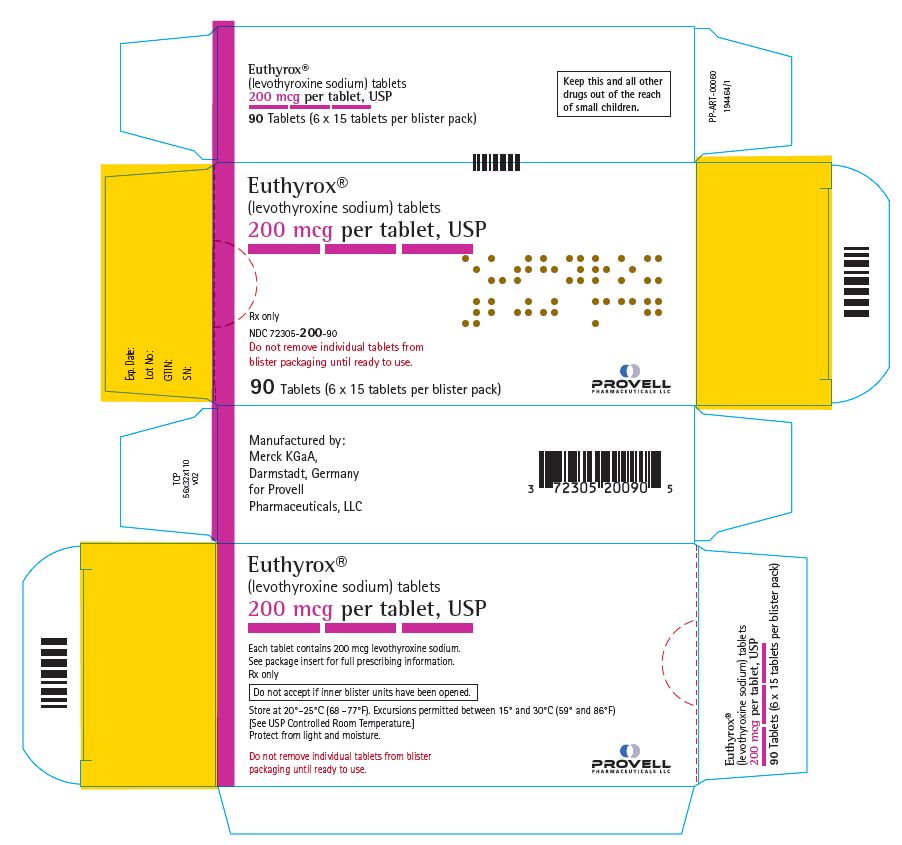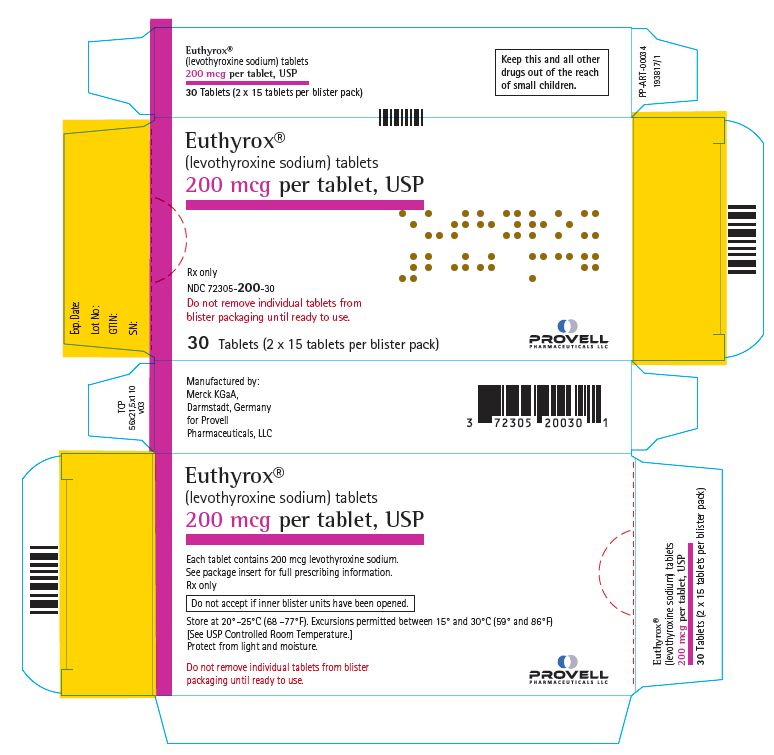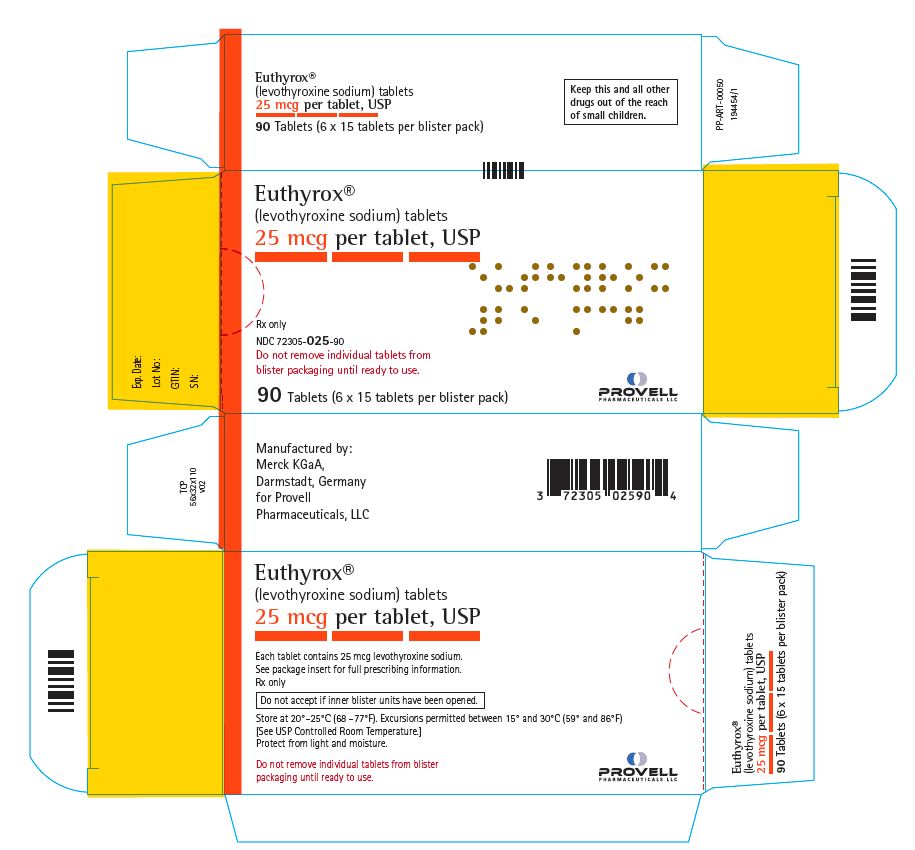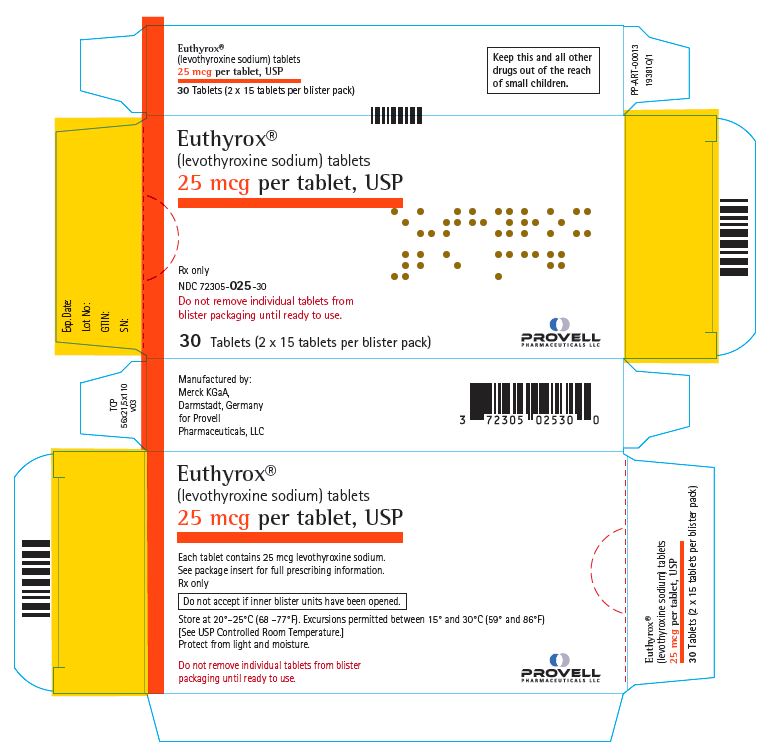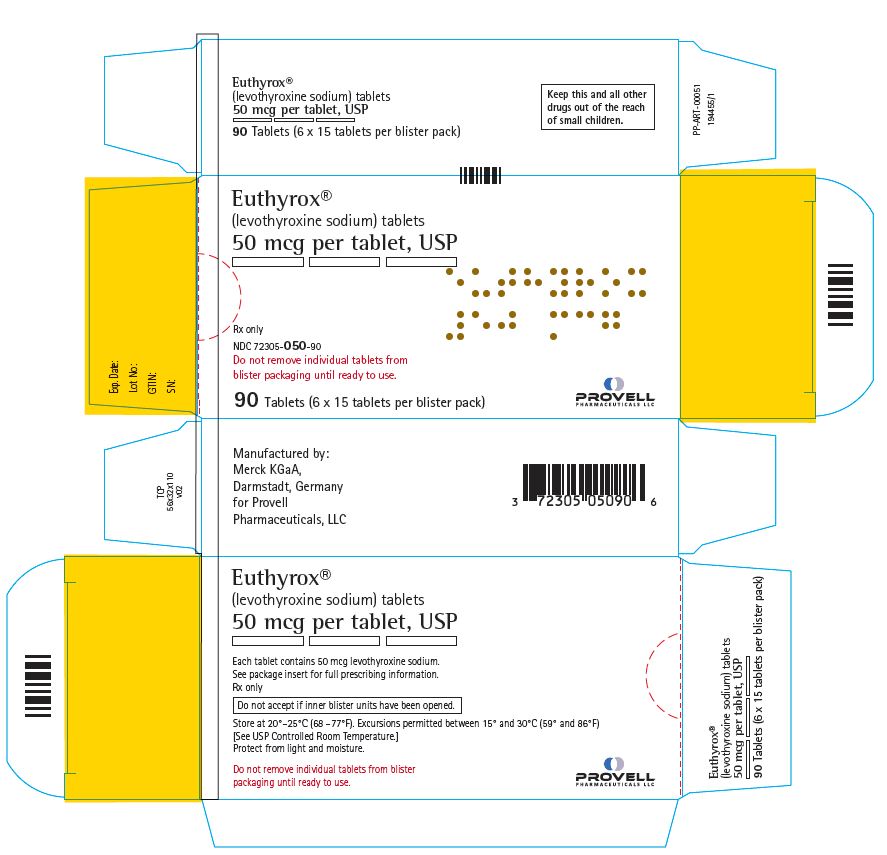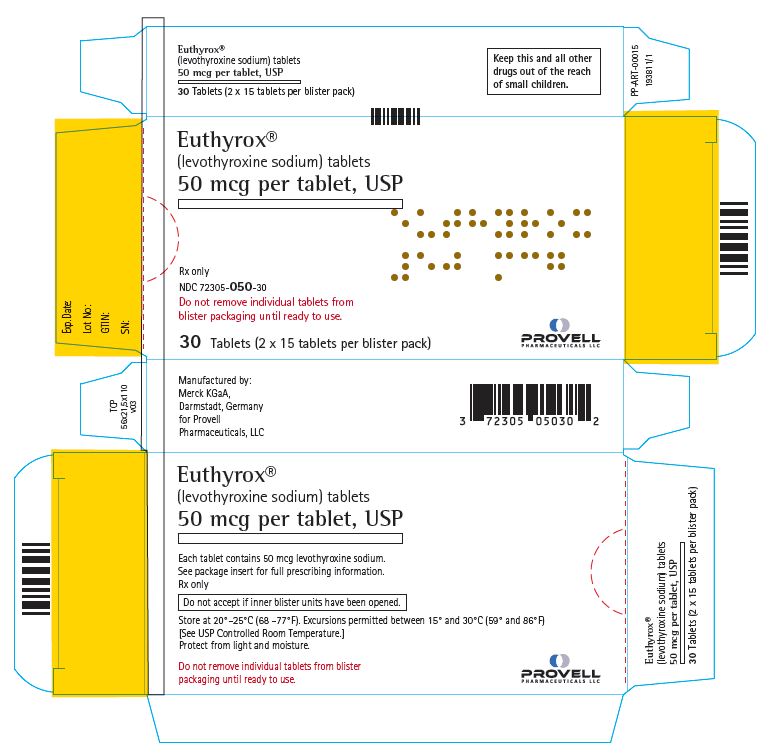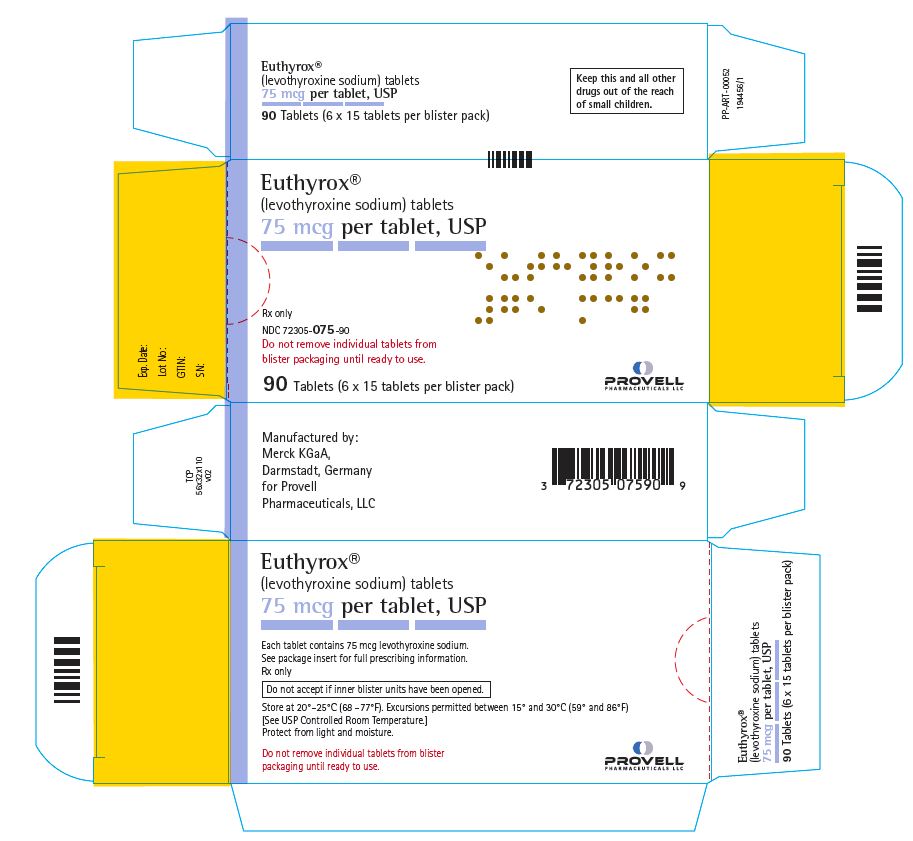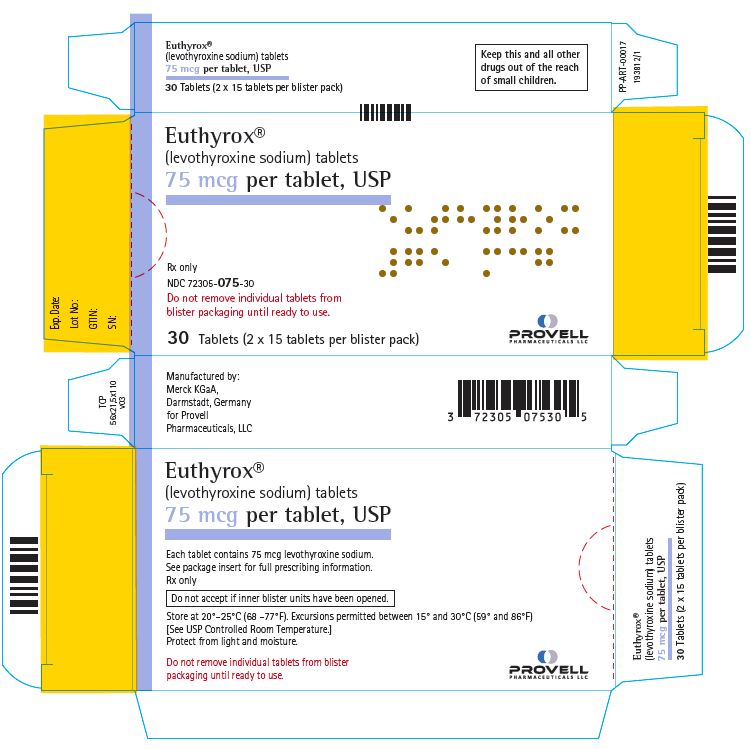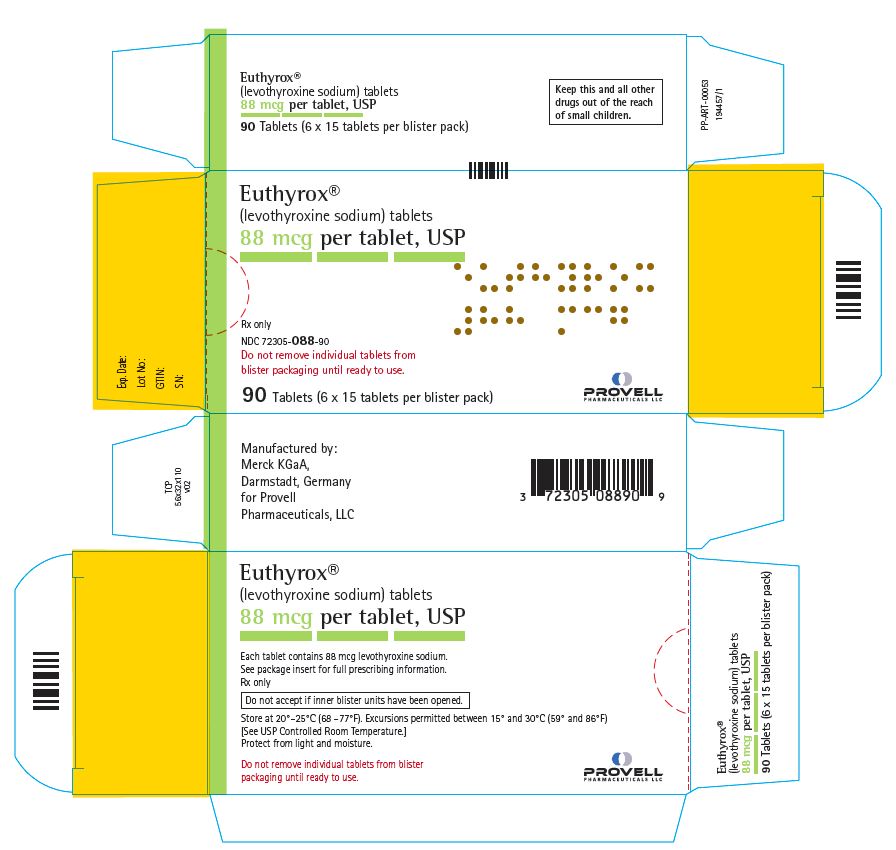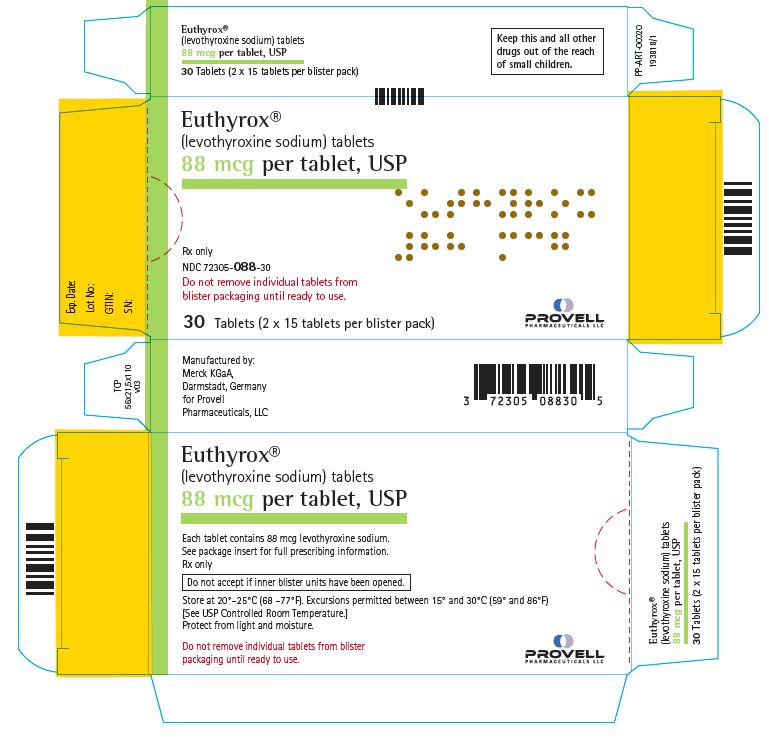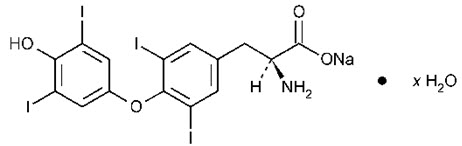 DRUG LABEL: EUTHYROX
NDC: 72305-025 | Form: TABLET
Manufacturer: Provell Pharmaceuticals, LLC
Category: prescription | Type: HUMAN PRESCRIPTION DRUG LABEL
Date: 20260127

ACTIVE INGREDIENTS: LEVOTHYROXINE SODIUM 25 ug/1 1
INACTIVE INGREDIENTS: Mannitol; STARCH, CORN; GELATIN, UNSPECIFIED; Croscarmellose sodium; ANHYDROUS CITRIC ACID; Magnesium Stearate

HIGHLIGHTS OF PRESCRIBING INFORMATION

These highlights do not include all the information needed to use EUTHYROX® safely and effectively. See full prescribing information for EUTHYROX.
EUTHYROX® (levothyroxine sodium) tablets, for oral use
Initial U.S. Approval: 2002

WARNING: NOT FOR TREATMENT OF OBESITY OR FOR WEIGHT LOSS

See full prescribing information for complete boxed warning.

- Thyroid hormones, including EUTHYROX, should not be used for the treatment of obesity or for weight loss.
- Doses beyond the range of daily hormonal requirements may produce serious or even life-threatening manifestations of toxicity (6, 10).

1 INDICATIONS AND USAGE

EUTHYROX is L-thyroxine (T4) indicated in pediatric and adult patients for:

- Hypothyroidism: As replacement in primary (thyroidal), secondary (pituitary), and tertiary (hypothalamic) congenital or acquired hypothyroidism. (1)
- Pituitary Thyrotropin (Thyroid-Stimulating Hormone, TSH) suppression: As an adjunct to surgery and radioiodine therapy in the management of thyrotropin-dependent well-differentiated thyroid cancer. (1)

Limitations of Use:

- Not indicated for suppression of benign thyroid nodules and nontoxic diffuse goiter in iodine-sufficient patients. (1)

- Not indicated for treatment of hypothyroidism during the recovery phase of subacute thyroiditis. (1)

2 DOSAGE AND ADMINISTRATION

- Administer once daily, on an empty stomach, one-half to one hour before breakfast. (2.1)
- Administer at least 4 hours before or after drugs that are known to interfere with absorption. (2.1)
- Evaluate the need for dose adjustments when regularly administering within one hour of certain foods that may affect absorption. (2.1)
- Starting dose depends on a variety of factors, including age, body weight, cardiovascular status, concomitant medical conditions (including pregnancy), concomitant medications, co-administered food, and the specific nature of the condition being treated. Peak therapeutic effect may not be attained for 4 to 6 weeks. (2.2)
- See full prescribing information for dosing in specific patient populations. (2.3)
- Adequacy of therapy determined with periodic monitoring of TSH and/or T4 as well as clinical status. (2.4)

3 DOSAGE FORMS AND STRENGTHS

Tablets: 25 mcg, 50 mcg, 75 mcg, 88 mcg, 100 mcg, 112 mcg, 125 mcg, 137 mcg, 150 mcg, 175 mcg, 200 mcg (3)

4 CONTRAINDICATIONS

- Uncorrected adrenal insufficiency. (4)

5 WARNINGS AND PRECAUTIONS

- Cardiac adverse reactions in the elderly and in patients with underlying cardiovascular disease: Initiate EUTHYROX at less than the full replacement dose because of the increased risk of cardiac adverse reactions, including atrial fibrillation. (2.3, 5.1, 8.5)
- Myxedema coma: Do not use oral thyroid hormone drug products to treat myxedema coma. (5.2)
- Acute adrenal crisis in patients with concomitant adrenal insufficiency: Treat with replacement glucocorticoids prior to initiation of EUTHYROX treatment. (5.3)
- Prevention of hyperthyroidism or incomplete treatment of hypothyroidism: Proper dose titration and careful monitoring is critical to prevent the persistence of hypothyroidism or the development of hyperthyroidism. (5.4)
- Worsening of diabetic control: Therapy in patients with diabetes mellitus may worsen glycemic control and result in increased antidiabetic agent or insulin requirements. Carefully monitor glycemic control after starting, changing, or discontinuing thyroid hormone therapy. (5.5)
- Decreased bone mineral density associated with thyroid hormone over-replacement: Over-replacement can increase bone resorption and decrease bone mineral density. Give the lowest effective dose. (5.6)

6 ADVERSE REACTIONS

Adverse reactions associated with EUTHYROX are primarily those of hyperthyroidism due to therapeutic overdosage: arrhythmias, myocardial infarction, dyspnea, muscle spasm, headache, nervousness, irritability, insomnia, tremors, muscle weakness, increased appetite, weight loss, diarrhea, heat intolerance, menstrual irregularities, and skin rash. (6)

To report SUSPECTED ADVERSE REACTIONS, contact Provell Pharmaceuticals, LLC at 1-888-899-7041 or FDA at1-800-FDA-1088 or www.fda.gov/medwatch.

7 DRUG INTERACTIONS

See full prescribing information for drugs that affect thyroid hormone pharmacokinetics and metabolism (e.g., absorption, synthesis, secretion, catabolism, protein binding, and target tissue response) and may alter the therapeutic response to EUTHYROX. (7)

8 USE IN SPECIFIC POPULATIONS

- Pregnancy may require the use of higher doses of EUTHYROX. (2.3, 8.1)

FULL PRESCRIBING INFORMATION

WARNING: NOT FOR TREATMENT OF OBESITY OR FOR WEIGHT LOSS

- Thyroid hormones, including EUTHYROX, either alone or with other therapeutic agents, should not be used for the treatment of obesity or for weight loss.
- In euthyroid patients, doses within the range of daily hormonal requirements are ineffective for weight reduction.
- Larger doses may produce serious or even life-threatening manifestations of toxicity, particularly when given in association with sympathomimetic amines such as those used for their anorectic effects [see Adverse Reactions (6), Drug Interactions (7.7), and Overdosage (10)].

1 INDICATIONS AND USAGE

Hypothyroidism

EUTHYROX is indicated in pediatric and adult patients as a replacement therapy in primary (thyroidal), secondary (pituitary), and tertiary (hypothalamic) congenital or acquired hypothyroidism.

Pituitary Thyrotropin (Thyroid-Stimulating Hormone, TSH) Suppression

EUTHYROX is indicated in pediatric and adult patients as an adjunct to surgery and radioiodine therapy in the management of thyrotropin-dependent well-differentiated thyroid cancer.

Limitations of Use:

- EUTHYROX is not indicated for suppression of benign thyroid nodules and nontoxic diffuse goiter in iodine-sufficient patients as there are no clinical benefits and overtreatment with EUTHYROX may induce hyperthyroidism [see Warnings and Precautions (5.4)].
- EUTHYROX is not indicated for treatment of hypothyroidism during the recovery phase of subacute thyroiditis.

2 DOSAGE AND ADMINISTRATION

2.1 General Administration Information

Administer EUTHYROX tablets orally as a single daily dose, on an empty stomach, one-half to one hour before breakfast.

Administer EUTHYROX at least 4 hours before or after drugs known to interfere with EUTHYROX absorption [see Drug Interactions (7.1)].

Evaluate the need for dose adjustments when regularly administering within one hour of certain foods that may affect EUTHYROX absorption [see Drug Interactions (7.9), Clinical Pharmacology (12.3)].

Administer EUTHYROX to infants and children who cannot swallow intact tablets by crushing the tablet, suspending the freshly crushed tablet in a small amount (5 mL to 10 mL or 1 teaspoon to 2 teaspoons) of water and immediately administering the suspension by spoon or dropper. Do not store the suspension. Do not administer in foods that decrease absorption of EUTHYROX, such as soybean-based infant formula [see Drug Interactions (7.9)].

2.2 General Principles of Dosing

The dose of EUTHYROX for hypothyroidism or pituitary TSH suppression depends on a variety of factors including: the patient's age, body weight, cardiovascular status, concomitant medical conditions (including pregnancy), concomitant medications, co-administered food and the specific nature of the condition being treated [see Dosage and Administration (2.3), Warnings and Precautions (5), Drug Interactions (7)]. Dosing must be individualized to account for these factors and dose adjustments made based on periodic assessment of the patient's clinical response and laboratory parameters [see Dosage and Administration (2.4)].

The peak therapeutic effect of a given dose of EUTHYROX may not be attained for 4 to 6 weeks.

2.3 Dosing in Specific Populations

Primary Hypothyroidism in Adults and in Adolescents in Whom Growth and Puberty Are Complete

Start EUTHYROX at the full replacement dose in otherwise healthy, non-elderly individuals who have been hypothyroid for only a short time (such as a few months). The average full replacement dose of EUTHYROX is approximately 1.6 mcg per kg per day (for example: 100 mcg per day to 125 mcg per day for a 70 kg adult).

Adjust the dose by 12.5 mcg to 25 mcg increments every 4 to 6 weeks until the patient is clinically euthyroid and the serum TSH returns to normal. Doses greater than 200 mcg per day are seldom required. An inadequate response to daily doses of greater than 300 mcg per day is rare and may indicate poor compliance, malabsorption, drug interactions, or a combination of these factors.

For elderly patients or patients with underlying cardiac disease, start with a dose of 12.5 mcg per day to 25 mcg per day. Increase the dose every 6 to 8 weeks, as needed until the patient is clinically euthyroid and the serum TSH returns to normal. The full replacement dose of EUTHYROX may be less than 1 mcg per kg per day in elderly patients.

In patients with severe longstanding hypothyroidism, start with a dose of 12.5 mcg per day to 25 mcg per day. Adjust the dose in 12.5 mcg to 25 mcg increments every 2 to 4 weeks until the patient is clinically euthyroid and the serum TSH level is normalized.

Secondary or Tertiary Hypothyroidism

Start EUTHYROX at the full replacement dose in otherwise healthy, non-elderly individuals. Start with a lower dose in elderly patients, patients with underlying cardiovascular disease or patients with severe longstanding hypothyroidism as described above. Serum TSH is not a reliable measure of EUTHYROX dose adequacy in patients with secondary or tertiary hypothyroidism and should not be used to monitor therapy. Use the serum free-T4 (L-thyroxine) level to monitor adequacy of therapy in this patient population. Titrate EUTHYROX dosing per above instructions until the patient is clinically euthyroid and the serum free-T4 level is restored to the upper half of the normal range.

Pediatric Dosage - Congenital or Acquired Hypothyroidism

The recommended daily dose of EUTHYROX in pediatric patients with hypothyroidism is based on body weight and changes with age as described in Table 1. Start EUTHYROX at the full daily dose in most pediatric patients. Start at a lower starting dose in newborns (0 to 3 months) at risk for cardiac failure and in children at risk for hyperactivity (see below). Monitor for clinical and laboratory response [see Dosage and Administration (2.4)].

Table 1. EUTHROX Dosing Guidelines for Pediatric Hypothyroidism
AGE | Daily Dose Per Kg Body Weight [The dose should be adjusted based on clinical response and laboratory parameters [see Dosage and Administration (2.4), Use in Specific Populations (8.4)]]
0 to 3 months | 10 mcg/kg daily to 15 mcg/kg daily
3 to 6 months | 8 mcg/kg daily to 10 mcg/kg daily
6 to 12 months | 6 mcg/kg daily to 8 mcg/kg daily
1 to 5 years | 5 mcg/kg daily to 6 mcg/kg daily
6 to 12 years | 4 mcg/kg daily to 5 mcg/kg daily
Greater than 12 years but growth and puberty incomplete | 2 mcg/kg daily to 3 mcg/kg daily
Growth and puberty complete | 1.6 mcg/kg daily

Newborns (0 to 3 months) at Risk for Cardiac Failure:

Consider a lower starting dose in newborns at risk for cardiac failure. Increase the dose every 4 to 6 weeks as needed based on clinical and laboratory response.

Pediatric Patients at Risk for Hyperactivity:

To minimize the risk of hyperactivity in pediatric patients, start at one-fourth the recommended full replacement dose, and increase on a weekly basis by one-fourth the full recommended replacement dose until the full recommended replacement dose is reached.

Pregnancy

Pre-existing Hypothyroidism: EUTHYROX dose requirements may increase during pregnancy. Measure serum TSH and free-T4 as soon as pregnancy is confirmed and, at a minimum, during each trimester of pregnancy. In patients with primary hypothyroidism, maintain serum TSH in the trimester-specific reference range. For patients with serum TSH above the normal trimester-specific range, increase the dose of EUTHYROX by 12.5 mcg daily to 25 mcg daily and measure TSH every 4 weeks until a stable EUTHYROX dose is reached and serum TSH is within the normal trimester-specific range. Reduce EUTHYROX dosage to pre-pregnancy levels immediately after delivery and measure serum TSH levels 4 to 8 weeks postpartum to ensure EUTHYROX dose is appropriate.

New Onset Hypothyroidism: Normalize thyroid function as rapidly as possible. In patients with moderate to severe signs and symptoms of hypothyroidism, start EUTHYROX at the full replacement dose (1.6 mcg per kg body weight per day). In patients with mild hypothyroidism (TSH less than 10 mIU per liter) start EUTHYROX at 1 mcg per kg body weight per day. Evaluate serum TSH every 4 weeks and adjust EUTHYROX dosage until a serum TSH is within the normal trimester-specific range [see Use in Specific Populations (8.1)].

TSH Suppression in Well-Differentiated Thyroid Cancer

The dose of EUTHYROX should target TSH levels within the desired therapeutic range. This may require a EUTHYROX dose of greater than 2 mcg per kg per day, depending on the target level for TSH suppression.

2.4 Monitoring TSH and/or Thyroxine (T4) Levels

Assess the adequacy of therapy by periodic assessment of laboratory tests and clinical evaluation. Persistent clinical and laboratory evidence of hypothyroidism despite an apparent adequate replacement dose of EUTHYROX may be evidence of inadequate absorption, poor compliance, drug interactions, or a combination of these factors.

Adults

In adult patients with primary hypothyroidism, monitor serum TSH levels after an interval of 6 to 8 weeks after any change in dose. In patients on a stable and appropriate replacement dose, evaluate clinical and biochemical response every 6 to 12 months and whenever there is a change in the patient's clinical status.

Pediatrics

In patients with congenital hypothyroidism, assess the adequacy of replacement therapy by measuring both serum TSH and total or free-T4. Monitor TSH and total or free-T4 in children as follows: 2 and 4 weeks after the initiation of treatment, 2 weeks after any change in dosage, and then every 3 to 12 months thereafter following dose stabilization until growth is completed. Poor compliance or abnormal values may necessitate more frequent monitoring. Perform routine clinical examination, including assessment of development, mental and physical growth, and bone maturation, at regular intervals.

While the general aim of therapy is to normalize the serum TSH level, TSH may not normalize in some patients due to in utero hypothyroidism causing a resetting of pituitary-thyroid feedback. Failure of the serum T4 to increase into the upper half of the normal range within 2 weeks of initiation of EUTHYROX therapy and/or of the serum TSH to decrease below 20 mIU per liter within 4 weeks may indicate the child is not receiving adequate therapy. Assess compliance, dose of medication administered, and method of administration prior to increasing the dose of EUTHYROX [see Warnings and Precautions (5.4) and Use in Specific Populations (8.4)])].

Secondary and Tertiary Hypothyroidism

Monitor serum free-T4 levels and maintain in the upper half of the normal range in these patients.

3 DOSAGE FORMS AND STRENGTHS

EUTHYROX tablets are uncoated, off-white, round and flat on both sides with a beveled edge, and a dividing score on both sides available as:

Tablet Strength | Tablet Markings
25 mcg | "EM" and "25"
50 mcg | "EM" and "50"
75 mcg | "EM" and "75"
88 mcg | "EM" and "88"
100 mcg | "EM" and "100"
112 mcg | "EM" and "112"
125 mcg | "EM" and "125"
137 mcg | "EM" and "137"
150 mcg | "EM" and "150"
175 mcg | "EM" and "175"
200 mcg | "EM" and "200"

4 CONTRAINDICATIONS

EUTHYROX is contraindicated in patients with uncorrected adrenal insufficiency [see Warnings and Precautions (5.3)].

5 WARNINGS AND PRECAUTIONS

5.1 Cardiac Adverse Reactions in the Elderly and in Patients with Underlying Cardiovascular Disease

Overtreatment with levothyroxine may cause an increase in heart rate, cardiac wall thickness, and cardiac contractility and may precipitate angina or arrhythmias, particularly in patients with cardiovascular disease and in elderly patients. Initiate EUTHYROX therapy in this population at lower doses than those recommended in younger individuals or in patients without cardiac disease [see Dosage and Administration (2.3), Use in Specific Populations (8.5)].

Monitor for cardiac arrhythmias during surgical procedures in patients with coronary artery disease receiving suppressive EUTHYROX therapy. Monitor patients receiving concomitant EUTHYROX and sympathomimetic agents for signs and symptoms of coronary insufficiency. If cardiovascular symptoms develop or worsen, reduce or withhold the EUTHYROX dose for one week and restart at a lower dose.

5.2 Myxedema Coma

Myxedema coma is a life-threatening emergency characterized by poor circulation and hypometabolism, and may result in unpredictable absorption of levothyroxine sodium from the gastrointestinal tract. Use of oral thyroid hormone drug products is not recommended to treat myxedema coma. Administer thyroid hormone products formulated for intravenous administration to treat myxedema coma.

5.3 Acute Adrenal Crisis in Patients with Concomitant Adrenal Insufficiency

Thyroid hormone increases metabolic clearance of glucocorticoids. Initiation of thyroid hormone therapy prior to initiating glucocorticoid therapy may precipitate an acute adrenal crisis in patients with adrenal insufficiency. Treat patients with adrenal insufficiency with replacement glucocorticoids prior to initiating treatment with EUTHYROX [see Contraindications (4)].

5.4 Prevention of Hyperthyroidism or Incomplete Treatment of Hypothyroidism

EUTHYROX has a narrow therapeutic index. Over- or under-treatment with EUTHYROX may have negative effects on growth and development, cardiovascular function, bone metabolism, reproductive function, cognitive function, emotional state, gastrointestinal function, and on glucose and lipid metabolism. Titrate the dose of EUTHYROX carefully and monitor response to titration to avoid these effects [see Dosage and Administration (2.4)]. Monitor for the presence of drug or food interactions when using EUTHYROX and adjust the dose as necessary [see Drug Interactions (7), Clinical Pharmacology (12.3)].

5.5 Worsening of Diabetic Control

Addition of levothyroxine therapy in patients with diabetes mellitus may worsen glycemic control and result in increased antidiabetic agent or insulin requirements. Carefully monitor glycemic control after starting, changing, or discontinuing EUTHYROX [see Drug Interactions (7.2)].

5.6 Decreased Bone Mineral Density Associated with Thyroid Hormone Over-Replacement

Increased bone resorption and decreased bone mineral density may occur as a result of levothyroxine over-replacement, particularly in post-menopausal women. The increased bone resorption may be associated with increased serum levels and urinary excretion of calcium and phosphorous, elevations in bone alkaline phosphatase, and suppressed serum parathyroid hormone levels. Administer the minimum dose of EUTHYROX that achieves the desired clinical and biochemical response to mitigate against this risk.

6 ADVERSE REACTIONS

Adverse reactions associated with EUTHYROX therapy are primarily those of hyperthyroidism due to therapeutic overdosage [see Warnings and Precautions (5), Overdosage (10)]. They include the following:

- General: fatigue, increased appetite, weight loss, heat intolerance, fever, excessive sweating
- Central Nervous System: headache, hyperactivity, nervousness, anxiety, irritability, emotional lability, insomnia
- Musculoskeletal: tremors, muscular weakness and cramps
- Cardiovascular: palpitations, tachycardia, arrhythmias, increased pulse and blood pressure, heart failure, angina, myocardial infarction, cardiac arrest
- Respiratory: dyspnea
- Gastrointestinal: diarrhea, vomiting, abdominal cramps and elevations in liver function tests
- Dermatologic: hair loss, flushing, rash
- Endocrine: decreased bone mineral density
- Reproductive: menstrual irregularities, impaired fertility

Seizures have been reported rarely with levothyroxine therapy.

Adverse Reactions in Pediatric Patients

Pseudotumor cerebri and slipped capital femoral epiphysis have been reported in pediatric patients receiving levothyroxine therapy. Overtreatment may result in craniosynostosis in infants and premature closure of the epiphyses in pediatric patients with resultant compromised adult height.

Hypersensitivity Reactions

Hypersensitivity reactions to inactive ingredients have occurred in patients treated with thyroid hormone products. These include urticaria, pruritus, skin rash, flushing, angioedema, various gastrointestinal symptoms (abdominal pain, nausea, vomiting and diarrhea), fever, arthralgia, serum sickness and wheezing. Hypersensitivity to levothyroxine itself is not known to occur.

7 DRUG INTERACTIONS

7.1 Drugs Known to Affect Thyroid Hormone Pharmacokinetics

Many drugs can exert effects on thyroid hormone pharmacokinetics (e.g. absorption, synthesis, secretion, catabolism, protein binding, and target tissue response) and may alter the therapeutic response to EUTHYROX (see Tables 2 – 5).

Table 2: Drugs That May Decrease T4 Absorption (Hypothyroidism)
Potential impact: Concurrent use may reduce the efficacy of EUTHYROX by binding and delaying or preventing absorption, potentially resulting in hypothyroidism
Drug or Drug Class | Effect
Calcium Carbonate Ferrous Sulfate | Calcium carbonate may form an insoluble chelate with levothyroxine, and ferrous sulfate likely forms a ferric-thyroxine complex. Administer EUTHYROX at least 4 hours apart from these agents.
Orlistat | Monitor patients treated concomitantly with orlistat and EUTHYROX for changes in thyroid function.
Bile Acid Sequestrants -Colesevelam -Cholestyramine -Colestipol Ion Exchange Resins -Kayexalate -Sevelamer | Bile acid sequestrants and ion exchange resins are known to decrease levothyroxine absorption. Administer EUTHYROX at least 4 hours prior to these drugs or monitor thyrotropin (TSH) levels.
Other drugs: Proton Pump Inhibitors Sucralfate Antacids - Aluminum & Magnesium Hydroxides - Simethicone | Gastric acidity is an essential requirement for adequate absorption of levothyroxine. Sucralfate, antacids and proton pump inhibitors may cause hypochlorhydria, affect intragastric pH, and reduce levothyroxine absorption. Monitor patients appropriately.

Table 3: Drugs That May Alter T4 and Triiodothyronine (T3) Serum Transport Without Affecting Free-Thyroxine (FT4) Concentration (Euthyroidism)
Drug or Drug Class | Effect
Clofibrate Estrogen-containing oral contraceptives Estrogens (oral) Heroin / Methadone 5-Fluorouracil Mitotane Tamoxifen | These drugs may increase serum thyroxine-binding globulin (TBG) concentration.
Androgens / Anabolic Steroids Asparaginase Glucocorticoids Slow-Release Nicotinic Acid | These drugs may decrease serum TBG concentration.
Potential impact (below): Administration of these agents with EUTHYROX results in an initial transient increase in FT4. Continued administration results in a decrease in serum T4 and normal FT4 and TSH concentrations.
Salicylates (> 2 g/day) | Salicylates inhibit binding of T4 and T3 to TBG and transthyretin. An initial increase in serum FT4 is followed by return of FT4 to normal levels with sustained therapeutic serum salicylate concentrations, although total T4 levels may decrease by as much as 30%.
Other drugs: Carbamazepine Furosemide (> 80 mg IV) Heparin Hydantoins Non-Steroidal Anti-inflammatory Drugs - Fenamates | These drugs may cause protein-binding site displacement. Furosemide has been shown to inhibit the protein binding of T4 to TBG and albumin, causing an increased free-T4 fraction in serum. Furosemide competes for T4-binding sites on TBG, prealbumin, and albumin, so that a single high dose can acutely lower the total T4 level. Phenytoin and carbamazepine reduce serum protein binding of levothyroxine, and total and free-T4 may be reduced by 20% to 40%, but most patients have normal serum TSH levels and are clinically euthyroid. Closely monitor thyroid hormone parameters.

Table 4: Drugs That May Alter Hepatic Metabolism of T4 (Hypothyroidism)
Potential impact: Stimulation of hepatic microsomal drug-metabolizing enzyme activity may cause increased hepatic degradation of levothyroxine, resulting in increased EUTHYROX requirements.
Drug or Drug Class | Effect
Phenobarbital Rifampin | Phenobarbital has been shown to reduce the response to thyroxine. Phenobarbital increases L-thyroxine metabolism by inducing uridine 5'-diphospho-glucuronosyltransferase (UGT) and leads to a lower T4 serum levels. Changes in thyroid status may occur if barbiturates are added or withdrawn from patients being treated for hypothyroidism. Rifampin has been shown to accelerate the metabolism of levothyroxine.

Table 5: Drugs That May Decrease Conversion of T4 to T3
Potential impact: Administration of these enzyme inhibitors decreases the peripheral conversion of T4 to T3, leading to decreased T3 levels. However, serum T4 levels are usually normal but may occasionally be slightly increased.
Drug or Drug Class | Effect
Beta-adrenergic antagonists (e.g., Propranolol > 160 mg/day) | In patients treated with large doses of propranolol (> 160 mg/day), T3 and T4 levels change, TSH levels remain normal, and patients are clinically euthyroid. Actions of particular beta-adrenergic antagonists may be impaired when the hypothyroid patient is converted to the euthyroid state.
Glucocorticoids (e.g., Dexamethasone ≥ 4 mg/day) | Short-term administration of large doses of glucocorticoids may decrease serum T3 concentrations by 30% with minimal change in serum T4 levels. However, long-term glucocorticoid therapy may result in slightly decreased T3 and T4 levels due to decreased TBG production (see Table 3 above).
Other: Amiodarone | Amiodarone inhibits peripheral conversion of levothyroxine (T4) to triiodothyronine (T3) and may cause isolated biochemical changes (increase in serum free-T4, and decrease or normal free-T3) in clinically euthyroid patients.

7.2 Antidiabetic Therapy

Addition of EUTHYROX therapy in patients with diabetes mellitus may worsen glycemic control and result in increased antidiabetic agent or insulin requirements. Carefully monitor glycemic control, especially when EUTHYROX is started, changed, or discontinued [see Warnings and Precautions (5.5)].

7.3 Oral Anticoagulants

EUTHYROX increases the response to oral anticoagulant therapy. Therefore, a decrease in the dose of anticoagulant may be warranted with correction of the hypothyroid state or when the EUTHYROX dose is increased. Closely monitor coagulation tests to permit appropriate and timely dosage adjustments.

7.4 Digitalis Glycosides

EUTHYROX may reduce the therapeutic effects of digitalis glycosides. Serum digitalis glycoside levels may decrease when a hypothyroid patient becomes euthyroid, necessitating an increase in the dose of digitalis glycosides.

7.5 Antidepressant Therapy

Concurrent use of tricyclic (e.g., amitriptyline) or tetracyclic (e.g., maprotiline) antidepressants and EUTHYROX may increase the therapeutic and toxic effects of both drugs, possibly due to increased receptor sensitivity to catecholamines. Toxic effects may include increased risk of cardiac arrhythmias and central nervous system stimulation. EUTHYROX may accelerate the onset of action of tricyclics. Administration of sertraline in patients stabilized on EUTHYROX may result in increased EUTHYROX requirements.

7.6 Ketamine

Concurrent use of ketamine and EUTHYROX may produce marked hypertension and tachycardia. Closely monitor blood pressure and heart rate in these patients.

7.7 Sympathomimetics

Concurrent use of sympathomimetics and EUTHYROX may increase the effects of sympathomimetics or thyroid hormone. Thyroid hormones may increase the risk of coronary insufficiency when sympathomimetic agents are administered to patients with coronary artery disease.

7.8 Tyrosine-Kinase Inhibitors

Concurrent use of tyrosine-kinase inhibitors such as imatinib may cause hypothyroidism. Closely monitor TSH levels in such patients.

7.9 Drug-Food Interactions

Consumption of certain foods may affect EUTHYROX absorption thereby necessitating adjustments in dosing [see Dosage and Administration (2.1)]. Soybean flour (infant formula), cottonseed meal, walnuts, and dietary fiber may bind and decrease the absorption of EUTHYROX from the gastrointestinal tract. Grapefruit juice may delay the absorption of levothyroxine and reduce its bioavailability.

7.10 Drug–Laboratory Test Interactions

Consider changes in TBG concentration when interpreting T4 and T3 values. Measure and evaluate unbound (free) hormone and/or determine the free-T4 index (FT4I) in this circumstance. Pregnancy, infectious hepatitis, estrogens, estrogen containing oral contraceptives, and acute intermittent porphyria increase TBG concentrations. Nephrosis, severe hypoproteinemia, severe liver disease, acromegaly, androgens and corticosteroids decrease TBG concentration. Familial hyper- or hypo-thyroxine binding globulinemias have been described, with the incidence of TBG deficiency approximating 1 in 9000.

8 USE IN SPECIFIC POPULATIONS

8.1 Pregnancy

Risk Summary

Experience with levothyroxine use in pregnant women, including data from post-marketing studies, have not reported increased rates of major birth defects or miscarriages (see Data). There are risks to the mother and fetus associated with untreated hypothyroidism in pregnancy. Since thyroid-stimulating hormone (TSH) levels may increase during pregnancy, TSH should be monitored and EUTHYROX dosage adjusted during pregnancy (see Clinical Considerations). There are no animal studies conducted with levothyroxine during pregnancy. EUTHYROX should not be discontinued during pregnancy and hypothyroidism diagnosed during pregnancy should be promptly treated.

The estimated background risk of major birth defects and miscarriage for the indicated population is unknown. In the U.S. general population, the estimated background risk of major birth defects and miscarriage in clinically recognized pregnancies is 2 to 4% and 15 to 20%, respectively.

Clinical Considerations

Disease-Associated Maternal and/or Embryo/Fetal Risk

Maternal hypothyroidism during pregnancy is associated with a higher rate of complications, including spontaneous abortion, gestational hypertension, pre-eclampsia, stillbirth, and premature delivery. Untreated maternal hypothyroidism may have an adverse effect on fetal neurocognitive development.

Dose Adjustments During Pregnancy and Postpartum Period

Pregnancy may increase EUTHYROX requirements. Serum TSH level should be monitored and the EUTHYROX dosage adjusted during pregnancy. Since postpartum TSH levels are similar to preconception values, the EUTHYROX dosage should return to the pre-pregnancy dose immediately after delivery [see Dosage and Administration (2.3)].

Data

Human Data

Levothyroxine is approved for use as a replacement therapy for hypothyroidism. There is a long experience of levothyroxine use in pregnant women, including data from post-marketing studies that have not reported increased rates of fetal malformations, miscarriages or other adverse maternal or fetal outcomes associated with levothyroxine use in pregnant women.

8.2 Lactation

Risk Summary

Limited published studies report that levothyroxine is present in human milk. However, there is insufficient information to determine the effects of levothyroxine on the breastfed infant and no available information on the effects of levothyroxine on milk production. Adequate levothyroxine treatment during lactation may normalize milk production in hypothyroid lactating mothers. The developmental and health benefits of breastfeeding should be considered along with the mother's clinical need for EUTHYROX and any potential adverse effects on the breastfed infant from EUTHYROX or from the underlying maternal condition.

8.4 Pediatric Use

The initial dose of EUTHYROX varies with age and body weight. Dosing adjustments are based on an assessment of the individual patient's clinical and laboratory parameters [see Dosage and Administration (2.3,2.4)].

In children in whom a diagnosis of permanent hypothyroidism has not been established, discontinue EUTHYROX administration for a trial period, but only after the child is at least 3 years of age. Obtain serum T4 and TSH levels at the end of the trial period, and use laboratory test results and clinical assessment to guide diagnosis and treatment, if warranted.

Congenital Hypothyroidism [see Dosage and Administration (2.3,2.4)]

Rapid restoration of normal serum T4 concentrations is essential for preventing the adverse effects of congenital hypothyroidism on intellectual development as well as on overall physical growth and maturation. Therefore, initiate EUTHYROX therapy immediately upon diagnosis. Levothyroxine is generally continued for life in these patients.

Closely monitor infants during the first 2 weeks of EUTHYROX therapy for cardiac overload, arrhythmias, and aspiration from avid suckling.

Closely monitor patients to avoid undertreatment or overtreatment. Undertreatment may have deleterious effects on intellectual development and linear growth. Overtreatment has been associated with craniosynostosis in infants, may adversely affect the tempo of brain maturation, and accelerate the bone age, with resultant premature closure of the epiphyses and compromised adult stature.

Acquired Hypothyroidism in Pediatric Patients

Closely monitor patients to avoid undertreatment and overtreatment. Undertreatment may result in poor school performance due to impaired concentration and slowed mentation and in reduced adult height. Overtreatment may accelerate the bone age and result in premature epiphyseal closure and compromised adult stature.

Treated children may manifest a period of catch-up growth, which may be adequate in some cases to normalize adult height. In children with severe or prolonged hypothyroidism, catch-up growth may not be adequate to normalize adult height.

8.5 Geriatric Use

Because of the increased prevalence of cardiovascular disease among the elderly, initiate EUTHYROX at less than the full replacement dose [see Warnings and Precautions (5.1) and Dosage and Administration (2.3)]. Atrial arrhythmias can occur in elderly patients. Atrial fibrillation is the most common of the arrhythmias observed with levothyroxine overtreatment in the elderly.

10 OVERDOSAGE

The signs and symptoms of overdosage are those of hyperthyroidism [See Warnings and Precautions (5.4) and Adverse Reactions (6)]. In addition, confusion and disorientation may occur. Cerebral embolism, shock, coma, and death have been reported. Seizures occurred in a 3 year-old child ingesting 3.6 mg levothyroxine. Symptoms may not necessarily be evident or may not appear until several days after ingestion of levothyroxine sodium.

Reduce the EUTHYROX dose or discontinue temporarily if signs or symptoms of overdosage occur. Initiate appropriate supportive treatment as dictated by the patient's medical status.

For current information on the management of poisoning or overdosage, contact the National Poison Control Center at 1-800-222-1222 or www.poison.org.

11 DESCRIPTION

EUTHYROX contains the active ingredient, levothyroxine, a synthetic crystalline levothyroxine (T4) in sodium salt form. It is chemically designated as L-3,3',5,5'-tetraiodothyronine monosodium hydrate. Synthetic T4 is identical in chemical structure to the T4 produced in the human thyroid gland. Levothyroxine sodium has the molecular formula C15H10I4NNaO4 ∙ xH2O, molecular weight of 798.85 (anhydrous), and structural formula as shown:

EUTHYROX tablets for oral administration are supplied in the following strengths: 25 mcg, 50 mcg, 75 mcg, 88 mcg, 100 mcg, 112 mcg, 125 mcg, 137 mcg, 150 mcg, 175 mcg, and 200 mcg. Inactive ingredients citric acid anhydrous, corn starch, gelatin, magnesium stearate, mannitol, sodium croscarmellose.

12 CLINICAL PHARMACOLOGY

12.1 Mechanism of Action

Thyroid hormones exert their physiologic actions through control of DNA transcription and protein synthesis. Triiodothyronine (T3) and L-thyroxine (T4) diffuse into the cell nucleus and bind to thyroid receptor proteins attached to DNA. This hormone nuclear receptor complex activates gene transcription and synthesis of messenger RNA and cytoplasmic proteins.

The physiological actions of thyroid hormones are produced predominantly by T3, the majority of which (approximately 80%) is derived from T4 by deiodination in peripheral tissues.

12.2 Pharmacodynamics

Oral levothyroxine sodium is a synthetic T4 hormone that exerts the same physiologic effect as endogenous T4, thereby maintaining normal T4 levels when a deficiency is present.

12.3 Pharmacokinetics

Absorption

Absorption of orally administered T4 from the gastrointestinal tract ranges from 40% to 80%. The majority of the levothyroxine dose is absorbed from the jejunum and upper ileum. The relative bioavailability of EUTHYROX tablets, compared to an equal nominal dose of oral levothyroxine sodium solution, is approximately 99%. T4 absorption is increased by fasting, and decreased in malabsorption syndromes and by certain foods such as soybeans. Dietary fiber decreases bioavailability of T4. Absorption may also decrease with age. In addition, many drugs and foods affect T4 absorption [see Drug Interactions (7)].

Distribution

Circulating thyroid hormones are greater than 99% bound to plasma proteins, including thyroxine-binding globulin (TBG), thyroxine-binding prealbumin (TBPA), and thyroxine-binding albumin (TBA), whose capacities and affinities vary for each hormone. The higher affinity of both TBG and TBPA for T4 partially explains the higher serum levels, slower metabolic clearance, and longer half-life of T4 compared to T3. Protein-bound thyroid hormones exist in reverse equilibrium with small amounts of free hormone. Only unbound hormone is metabolically active. Many drugs and physiologic conditions affect the binding of thyroid hormones to serum proteins [see Drug Interactions (7)]. Thyroid hormones do not readily cross the placental barrier [see Use in Specific Populations (8.1)].

Elimination

Metabolism

T4 is slowly eliminated (Table 6). The major pathway of thyroid hormone metabolism is through sequential deiodination. Approximately 80% of circulating T3 is derived from peripheral T4 by monodeiodination. The liver is the major site of degradation for both T4 and T3, with T4 deiodination also occurring at a number of additional sites, including the kidney and other tissues. Approximately 80% of the daily dose of T4 is deiodinated to yield equal amounts of T3 and reverse T3 (rT3). T3 and rT3 are further deiodinated to diiodothyronine. Thyroid hormones are also metabolized via conjugation with glucuronides and sulfates and excreted directly into the bile and gut where they undergo enterohepatic recirculation.

Table 6: Pharmacokinetic Parameters of Thyroid Hormones in Euthyroid Patients
Hormone | Ratio in Thyroglobulin | Biologic Potency | t½ (days) | Protein Binding (%) [Includes TBG, TBPA, and TBA]
Levothyroxine (T4) | 10–20 | 1 | 6–7 [3 to 4 days in hyperthyroidism, 9 to 10 days in hypothyroidism] | 99.96
Liothyronine (T3) | 1 | 4 | ≤ 2 | 99.5

Excretion

Thyroid hormones are primarily eliminated by the kidneys. A portion of the conjugated hormone reaches the colon unchanged and is eliminated in the feces. Approximately 20% of T4 is eliminated in the stool. Urinary excretion of T4 decreases with age.

13 NONCLINICAL TOXICOLOGY

13.1 Carcinogenesis, Mutagenesis, Impairment of Fertility

Animal studies have not been performed to evaluate the carcinogenic potential, mutagenic potential, or effects on fertility of levothyroxine.

16 HOW SUPPLIED/STORAGE AND HANDLING

EUTHYROX (levothyroxine sodium) tablets are uncoated, off-white, round and flat on both sides with a beveled edge, and a dividing score on both sides available as:

Tablet Strength | Tablet Markings | Carton Marking; and Blister; Packaging Color | NDC 30-count carton | NDC 90-count carton
25 mcg | “EM” and “25” | Orange | NDC 72305-025-30 | NDC 72305-025-90
50 mcg | “EM” and “50” | White | NDC 72305-050-30 | NDC 72305-050-90
75 mcg | “EM” and “75” | Purple | NDC 72305-075-30 | NDC 72305-075-90
88 mcg | “EM” and “88” | Olive | NDC 72305-088-30 | NDC 72305-088-90
100 mcg | “EM” and “100” | Yellow | NDC 72305-100-30 | NDC 72305-100-90
112 mcg | “EM” and “112” | Rose | NDC 72305-112-30 | NDC 72305-112-90
125 mcg | “EM” and “125” | Brown | NDC 72305-125-30 | NDC 72305-125-90
137 mcg | “EM” and “137” | Turquoise | NDC 72305-137-30 | NDC 72305-137-90
150 mcg | “EM” and “150” | Blue | NDC 72305-150-30 | NDC 72305-150-90
175 mcg | “EM” and “175” | Lilac | NDC 72305-175-30 | NDC 72305-175-90
200 mcg | “EM” and “200” | Pink | NDC 72305-200-30 | NDC 72305-200-90

Each 30-count carton contains 30 tablets with 2 blister packs. Each 90-count carton contains 90 tablets with 6 blister packs. Each blister pack contains 15 tablets placed in individual cavities.

STORAGE AND HANDLING

Store between 20°C to 25°C (68°F to 77°F), with excursions permitted between 15°C to 30°C (59°F to 86°F). Protect from light and moisture, avoid heat. Do not separate the individual cavities containing the tablet from the intact blister and do not remove the individual tablets from blister packaging until ready to use.

17 PATIENT COUNSELING INFORMATION

Inform the patient of the following information to aid in the safe and effective use of EUTHYROX:

Dosing and Administration

- Instruct patients to take EUTHYROX only as directed by their healthcare provider.
- Instruct patients to take EUTHYROX as a single dose, preferably on an empty stomach, one-half to one hour before breakfast.
- Inform patients that agents such as iron and calcium supplements and antacids can decrease the absorption of levothyroxine. Instruct patients not to take EUTHYROX tablets within 4 hours of these agents.
- Instruct patients to notify their healthcare provider if they are pregnant or breastfeeding or are thinking of becoming pregnant while taking EUTHYROX.

Important Information

- Inform patients that it may take several weeks before they notice an improvement in symptoms.
- Inform patients that the levothyroxine in EUTHYROX is intended to replace a hormone that is normally produced by the thyroid gland. Generally, replacement therapy is to be taken for life.
- Inform patients that EUTHYROX should not be used as a primary or adjunctive therapy in a weight control program.
- Instruct patients to notify their healthcare provider if they are taking any other medications, including prescription and over-the-counter preparations.
- Instruct patients to notify their physician of any other medical conditions they may have, particularly heart disease, diabetes, clotting disorders, and adrenal or pituitary gland problems, as the dose of medications used to control these other conditions may need to be adjusted while they are taking EUTHYROX. If they have diabetes, instruct patients to monitor their blood and/or urinary glucose levels as directed by their physician and immediately report any changes to their physician. If patients are taking anticoagulants, their clotting status should be checked frequently.
- Instruct patients to notify their physician or dentist that they are taking EUTHYROX prior to any surgery.

Adverse Reactions

- Instruct patients to notify their healthcare provider if they experience any of the following symptoms: rapid or irregular heartbeat, chest pain, shortness of breath, leg cramps, headache, nervousness, irritability, sleeplessness, tremors, change in appetite, weight gain or loss, vomiting, diarrhea, excessive sweating, heat intolerance, fever, changes in menstrual periods, hives or skin rash, or any other unusual medical event.
- Inform patients that partial hair loss may occur rarely during the first few months of EUTHYROX therapy, but this is usually temporary.

Rx Only

Manufactured by:
Merck KGaA
Frankfurter Straße 250
64293 Darmstadt, Germany

Marketed by:
Provell Pharmaceuticals, LLC
1801 Horseshoe Pike – Suite 1
Honey Brook, PA 19344 US

Revised: 04/2022

PP-ART-00012

© 2021 Provell Pharmaceuticals, LLC

PRINCIPAL DISPLAY PANEL - 25 mcg Tablet Blister Pack Carton

Euthyrox
(levothyroxine sodium) tablets
25 mcg per tablet, USP

Rx only

NDC 72305-025-30

Do not remove individual tablets from
blister packaging until ready to use.

30 Tablets (2 x 15 tablets per blister pack)

PROVELL
PHARMACEUTICALS LLC

PRINCIPAL DISPLAY PANEL - 50 mcg Tablet Blister Pack Carton

Euthyrox
(levothyroxine sodium) tablets
50 mcg per tablet, USP

Rx only

NDC 72305-050-30

Do not remove individual tablets from
blister packaging until ready to use.

30 Tablets (2 x 15 tablets per blister pack)

PROVELL
PHARMACEUTICALS LLC

PRINCIPAL DISPLAY PANEL - 75 mcg Tablet Blister Pack Carton

Euthyrox
(levothyroxine sodium) tablets
75 mcg per tablet, USP

Rx only

NDC 72305-075-30

Do not remove individual tablets from
blister packaging until ready to use.

30 Tablets (2 x 15 tablets per blister pack)

PROVELL
PHARMACEUTICALS LLC

PRINCIPAL DISPLAY PANEL - 88 mcg Tablet Blister Pack Carton

Euthyrox
(levothyroxine sodium) tablets
88 mcg per tablet, USP

Rx only

NDC 72305-088-30

Do not remove individual tablets from
blister packaging until ready to use.

30 Tablets (2 x 15 tablets per blister pack)

PROVELL
PHARMACEUTICALS LLC

PRINCIPAL DISPLAY PANEL - 100 mcg Tablet Blister Pack Carton

Euthyrox
(levothyroxine sodium) tablets
100 mcg per tablet, USP

Rx only

NDC 72305-100-30

Do not remove individual tablets from
blister packaging until ready to use.

30 Tablets (2 x 15 tablets per blister pack)

PROVELL
PHARMACEUTICALS LLC

PRINCIPAL DISPLAY PANEL - 112 mcg Tablet Blister Pack Carton

Euthyrox
(levothyroxine sodium) tablets
112 mcg per tablet, USP

Rx only

NDC 72305-112-30

Do not remove individual tablets from
blister packaging until ready to use.

30 Tablets (2 x 15 tablets per blister pack)

PROVELL
PHARMACEUTICALS LLC

PRINCIPAL DISPLAY PANEL - 125 mcg Tablet Blister Pack Carton

Euthyrox
(levothyroxine sodium) tablets
125 mcg per tablet, USP

Rx only

NDC 72305-125-30

Do not remove individual tablets from
blister packaging until ready to use.

30 Tablets (2 x 15 tablets per blister pack)

PROVELL
PHARMACEUTICALS LLC

PRINCIPAL DISPLAY PANEL - 137 mcg Tablet Blister Pack Carton

Euthyrox
(levothyroxine sodium) tablets
137 mcg per tablet, USP

Rx only

NDC 72305-137-30

Do not remove individual tablets from
blister packaging until ready to use.

30 Tablets (2 x 15 tablets per blister pack)

PROVELL
PHARMACEUTICALS LLC

PRINCIPAL DISPLAY PANEL - 150 mcg Tablet Blister Pack Carton

Euthyrox
(levothyroxine sodium) tablets
150 mcg per tablet, USP

Rx only

NDC 72305-150-30

Do not remove individual tablets from
blister packaging until ready to use.

30 Tablets (2 x 15 tablets per blister pack)

PROVELL
PHARMACEUTICALS LLC

PRINCIPAL DISPLAY PANEL - 175 mcg Tablet Blister Pack Carton

Euthyrox
(levothyroxine sodium) tablets
175 mcg per tablet, USP

Rx only

NDC 72305-175-30

Do not remove individual tablets from
blister packaging until ready to use.

30 Tablets (2 x 15 tablets per blister pack)

PROVELL
PHARMACEUTICALS LLC

PRINCIPAL DISPLAY PANEL - 200 mcg Tablet Blister Pack Carton

Euthyrox
(levothyroxine sodium) tablets
200 mcg per tablet, USP

Rx only

NDC 72305-200-30

Do not remove individual tablets from
blister packaging until ready to use.

30 Tablets (2 x 15 tablets per blister pack)

PROVELL
PHARMACEUTICALS LLC

PRINCIPAL DISPLAY PANEL - 25 mcg Tablet Blister Pack Carton

Euthyrox®
(levothyroxine sodium) tablets
25 mcg per tablet, USP

Rx only

NDC 72305-025-90

Do not remove individual tablets from
blister packaging until ready to use.

90 Tablets (6 x 15 tablets per blister pack)

PROVELL
PHARMACEUTICALS LLC

PRINCIPAL DISPLAY PANEL - 50 mcg Tablet Blister Pack Carton

Euthyrox®
(levothyroxine sodium) tablets
50 mcg per tablet, USP

Rx only

NDC 72305-050-90

Do not remove individual tablets from
blister packaging until ready to use.

90 Tablets (6 x 15 tablets per blister pack)

PROVELL
PHARMACEUTICALS LLC

PRINCIPAL DISPLAY PANEL - 75 mcg Tablet Blister Pack Carton

Euthyrox®
(levothyroxine sodium) tablets
75 mcg per tablet, USP

Rx only

NDC 72305-075-90

Do not remove individual tablets from
blister packaging until ready to use.

90 Tablets (6 x 15 tablets per blister pack)

PROVELL
PHARMACEUTICALS LLC

PRINCIPAL DISPLAY PANEL - 88 mcg Tablet Blister Pack Carton

Euthyrox®
(levothyroxine sodium) tablets
88 mcg per tablet, USP

Rx only

NDC 72305-088-90

Do not remove individual tablets from
blister packaging until ready to use.

90 Tablets (6 x 15 tablets per blister pack)

PROVELL
PHARMACEUTICALS LLC

PRINCIPAL DISPLAY PANEL - 100 mcg Tablet Blister Pack Carton

Euthyrox®
(levothyroxine sodium) tablets
100 mcg per tablet, USP

Rx only

NDC 72305-100-90

Do not remove individual tablets from
blister packaging until ready to use.

90 Tablets (6 x 15 tablets per blister pack)

PROVELL
PHARMACEUTICALS LLC

PRINCIPAL DISPLAY PANEL - 112 mcg Tablet Blister Pack Carton

Euthyrox®
(levothyroxine sodium) tablets
112 mcg per tablet, USP

Rx only

NDC 72305-112-90

Do not remove individual tablets from
blister packaging until ready to use.

90 Tablets (6 x 15 tablets per blister pack)

PROVELL
PHARMACEUTICALS LLC

PRINCIPAL DISPLAY PANEL - 125 mcg Tablet Blister Pack Carton

Euthyrox®
(levothyroxine sodium) tablets
125 mcg per tablet, USP

Rx only

NDC 72305-125-90

Do not remove individual tablets from
blister packaging until ready to use.

90 Tablets (6 x 15 tablets per blister pack)

PROVELL
PHARMACEUTICALS LLC

PRINCIPAL DISPLAY PANEL - 137 mcg Tablet Blister Pack Carton

Euthyrox®
(levothyroxine sodium) tablets
137 mcg per tablet, USP

Rx only

NDC 72305-137-90

Do not remove individual tablets from
blister packaging until ready to use.

90 Tablets (6 x 15 tablets per blister pack)

PROVELL
PHARMACEUTICALS LLC

PRINCIPAL DISPLAY PANEL - 150 mcg Tablet Blister Pack Carton

Euthyrox®
(levothyroxine sodium) tablets
150 mcg per tablet, USP

Rx only

NDC 72305-150-90

Do not remove individual tablets from
blister packaging until ready to use.

90 Tablets (6 x 15 tablets per blister pack)

PROVELL
PHARMACEUTICALS LLC

PRINCIPAL DISPLAY PANEL - 175 mcg Tablet Blister Pack Carton

Euthyrox®
(levothyroxine sodium) tablets
175 mcg per tablet, USP

Rx only

NDC 72305-175-90

Do not remove individual tablets from
blister packaging until ready to use.

90 Tablets (6 x 15 tablets per blister pack)

PROVELL
PHARMACEUTICALS LLC

PRINCIPAL DISPLAY PANEL - 200 mcg Tablet Blister Pack Carton

Euthyrox®
(levothyroxine sodium) tablets
200 mcg per tablet, USP

Rx only

NDC 72305-200-90

Do not remove individual tablets from
blister packaging until ready to use.

90 Tablets (6 x 15 tablets per blister pack)

PROVELL
PHARMACEUTICALS LLC